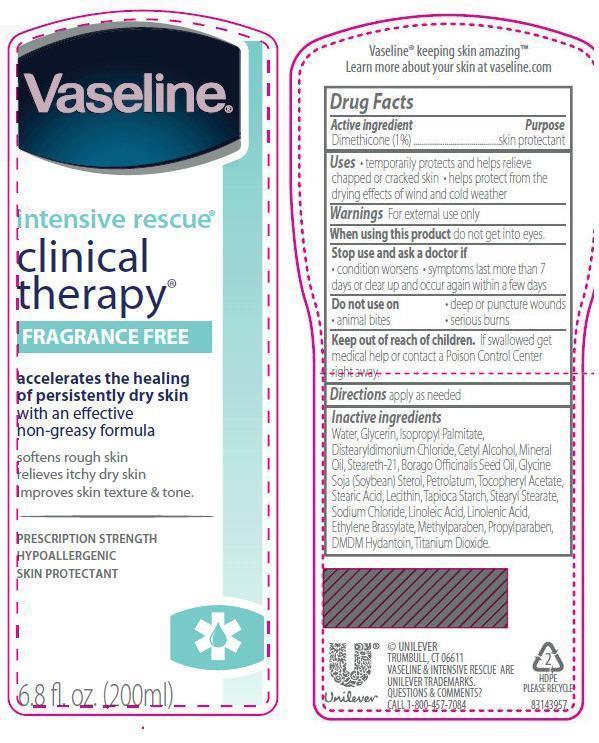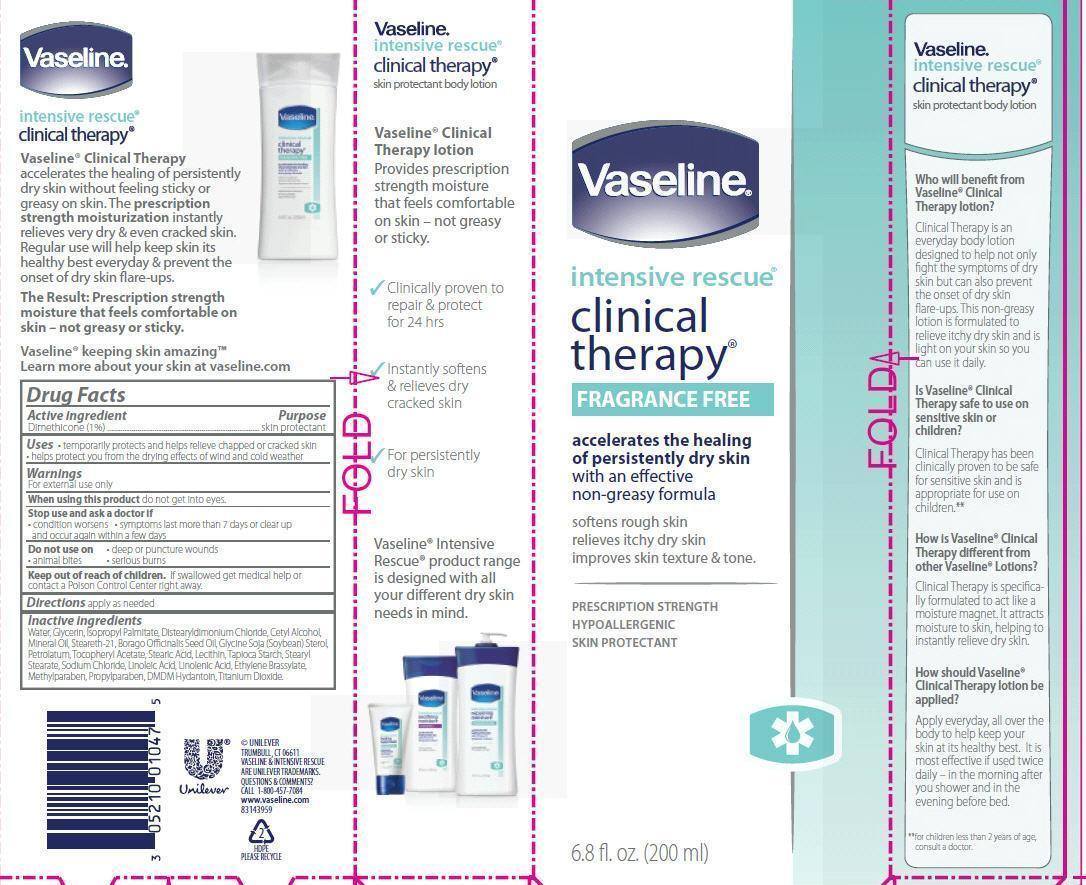 DRUG LABEL: Vaseline
NDC: 64942-1038 | Form: LOTION
Manufacturer: Conopco Inc. d/b/a Unilever
Category: otc | Type: HUMAN OTC DRUG LABEL
Date: 20121115

ACTIVE INGREDIENTS: DIMETHICONE 1 g/100 mL
INACTIVE INGREDIENTS: WATER; GLYCERIN; ISOPROPYL PALMITATE; DISTEARYLDIMONIUM CHLORIDE; CETYL ALCOHOL; MINERAL OIL; STEARETH-21; BORAGO OFFICINALIS SEED; PETROLATUM; .ALPHA.-TOCOPHEROL ACETATE; STEARIC ACID; LECITHIN, SOYBEAN; STARCH, TAPIOCA; STEARYL STEARATE; SODIUM CHLORIDE; LINOLEIC ACID; LINOLENIC ACID; DMDM HYDANTOIN; METHYLPARABEN; PROPYLPARABEN; TITANIUM DIOXIDE

Vaseline Intensive Rescue Clinical Therapy Fragrance Free Lotion

Active ingredient

Dimethicone (1%)

Purpose

skin protectant

Uses

● temporarily protects and helps relieve chapped or cracked skin● helps protect from the drying effects of wind and cold weather

Warnings

For External Use Only

When using this product do not get into eyes.

Stop use and ask a doctor if ● condition worsens ● symptoms last more than 7 days or clear up and occur again within a few days.

Do not use on ● deep or puncture wounds ● animal bites ● serious burns

Keep out of reach of children. If swallowed get medical help or contact a Poison Control Center right away.

Directions

apply as needed

Inactive ingredients

Water, Glycerin, Isopropyl Palmitate, Distearyldimonium Chloride, Cetyl Alcohol, Mineral Oil, Steareth-21, Borago Officinalis Seed Oil, Glycine Soja (Soybean) Sterol, Petrolatum, Tocopheryl Acetate, Stearic Acid, Lecithin, Tapioca Starch, Stearyl Stearate, Sodium Chloride, Linoleic Acid, Linolenic Acid, Ethylene Brassylate, Methylparaben, Propylparaben, DMDM Hydantoin, Titanium Dioxide.

QUESTIONS & COMMENTS? Call 1-800-457-7084